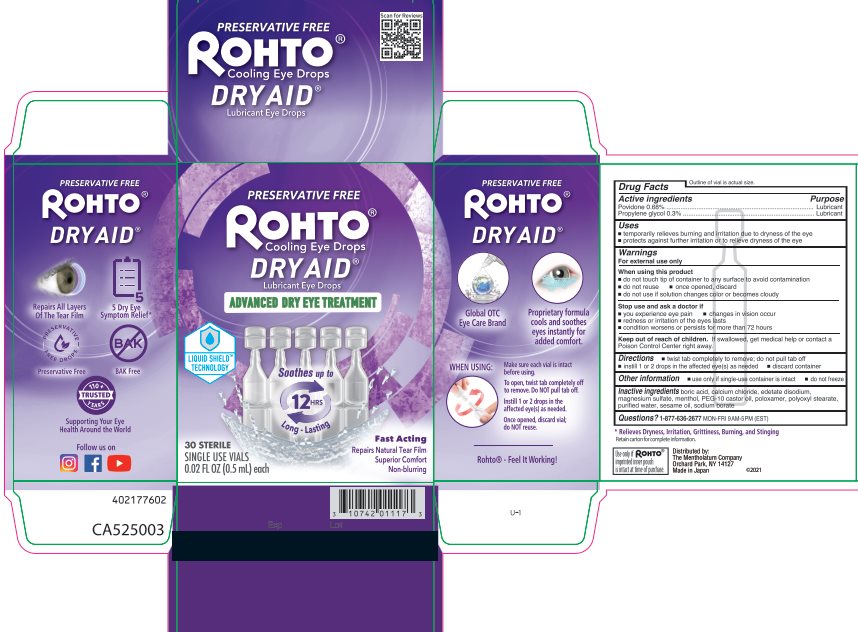 DRUG LABEL: Rohto
NDC: 10742-8161 | Form: LIQUID
Manufacturer: The Mentholatum Company
Category: otc | Type: HUMAN OTC DRUG LABEL
Date: 20241217

ACTIVE INGREDIENTS: POVIDONE, UNSPECIFIED 6.8 mg/1 mL; PROPYLENE GLYCOL 3 mg/1 mL
INACTIVE INGREDIENTS: BORIC ACID; CALCIUM CHLORIDE; EDETATE DISODIUM; MAGNESIUM SULFATE ANHYDROUS; RACEMENTHOL; POLYOXYL 35 CASTOR OIL; PEG/PPG-105/5 COPOLYMER; POLYOXYL 40 STEARATE; WATER; SESAME OIL; SODIUM BORATE

Drug Facts - Preservative Free Dry Aid

Active ingredient

Povidone 0.68%

Propylene glycol 0.3%

Purpose

Povidone – Lubricant

Propylene glycol - Lubricant

Uses

- temporarily relieves burning and irritation due to dryness of the eye
- protects against further irritation or to relieve dryness of the eye

Warnings

For external use only

When using this product

- do not touch tip of container to any surface to avoid contamination
- do not reuse
- once opened, discard
- do not use if solution changes color or becomes cloudy

Stop use and ask a doctor if

- you experience eye pain
- changes in vision occur
- redness or irritation of the eyes lasts
- condition worsens or persists for more than 72 hours

Keep out of reach of children.

If swallowed, get medical help or contact a Poison Control Center right away.

Directions

- twist tab completely to remove; do not pull tab off
- instill 1 or 2 drops in the affected eye(s) as needed
- discard container

Other information

- use only if single-use container is intact
- do not freeze

Inactive ingredients

boric acid, calcium chloride, edetate disodium, magnesium sulfate, menthol, PEG-10 castor oil, poloxamer, polyoxyl stearate, purified water, sesame oil, sodium borate

Questions?

1-877-636-2677 MON-FRI 9AM-5PM (EST)